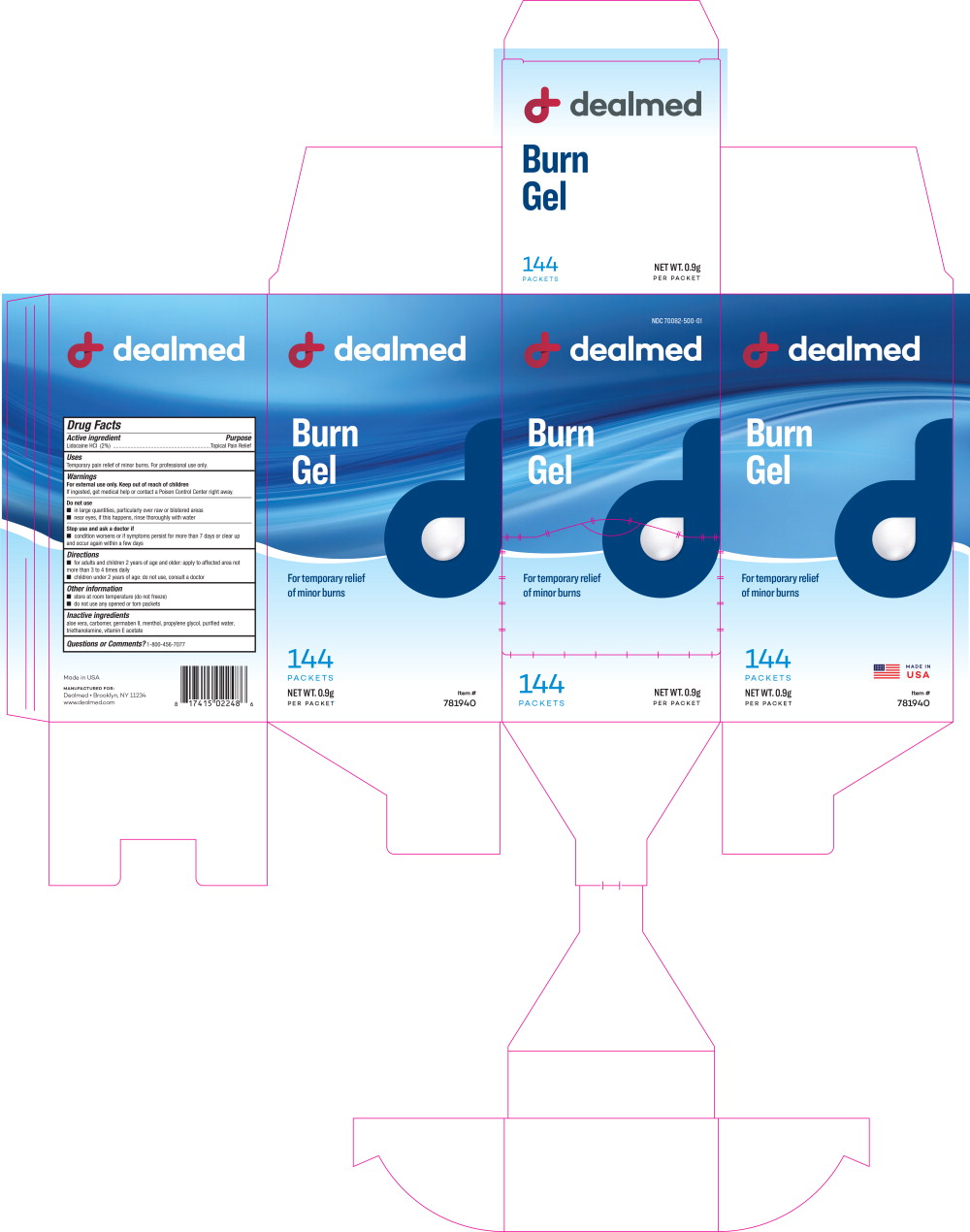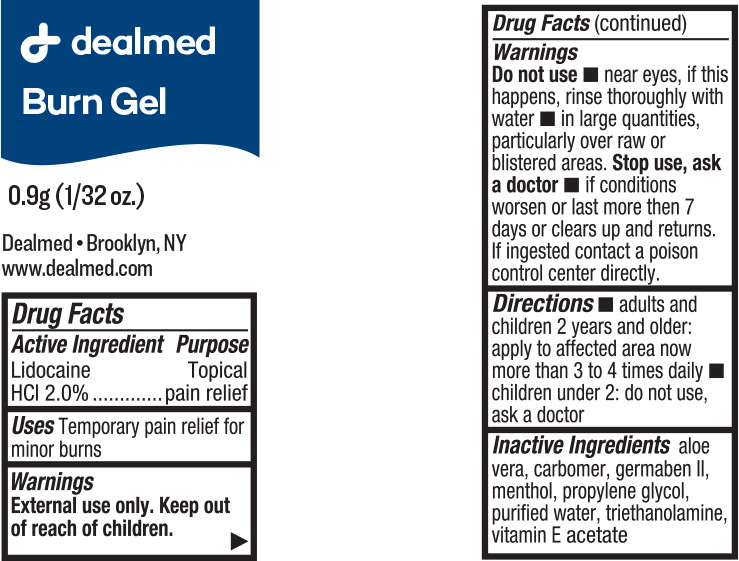 DRUG LABEL: Lidocaine Hydrochloride
NDC: 70082-500 | Form: GEL
Manufacturer: Dealmed Medical Supplies LLC
Category: otc | Type: HUMAN OTC DRUG LABEL
Date: 20220308

ACTIVE INGREDIENTS: Lidocaine Hydrochloride 18 mg/1 g
INACTIVE INGREDIENTS: aloe vera leaf; propylene glycol; diazolidinyl urea; water; menthol; .alpha.-tocopherol acetate; trolamine

Drug Facts

Active ingredient

Lidocaine HCI (2%)

Purpose

Topical Pain Relief

Uses

Temporary pain relief of minor burns. For professional use only.

Warnings

For external use only.

Keep out of reach of children

If ingested, get medical help or contact a Poison Control Center right away.

Do not use

- in large quantities, particularly over raw or blistered areas
- near eyes, if this happens, rinse thoroughly with water

Stop use and ask a doctor if

- condition worsens or if symptoms persist for more than 7 days or clear up and occur again within a few days

Directions

- for adults and children 2 years of age and older: apply to affected area not more than 3 to 4 times daily
- children under 2 years of age: do not use, consult a doctor

Other information

- store at room temperature (do not freeze)
- do not use any opened or torn packets

Inactive ingredients

aloe vera, carbomer, germaben II, menthol, propylene glycol, purified water, triethanolamine, vitamin E acetate

Questions or Comments?

1-800-456-7077

Principal Display Panel - 0.9g Box Label

NDC 70082-500-01

dealmed

Burn
Gel

For temporary relief
of minor burns

144
PACKETS

NET WT. 0.9g
PER PACKET

Principal Display Panel - 0.9g Pouch Label

dealmed

Burn Gel

0.9g (1/32 oz.)

Dealmed • Brooklyn, NY

www.dealmed.com